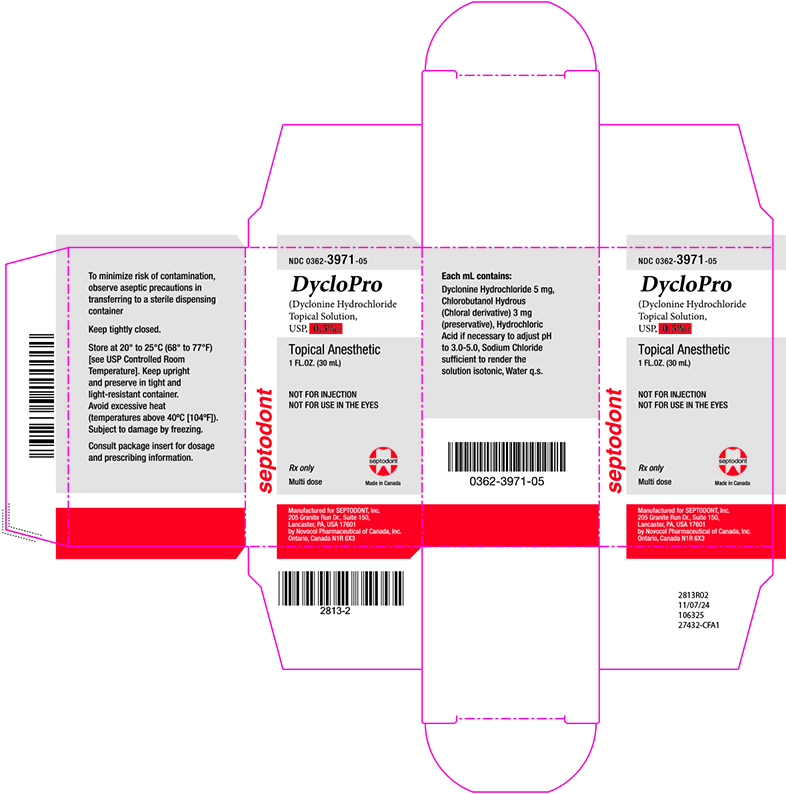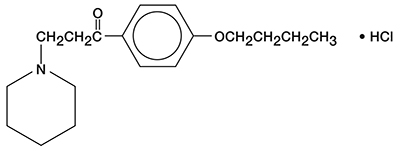 DRUG LABEL: DycloPro
NDC: 0362-3971 | Form: SOLUTION
Manufacturer: Septodont Inc
Category: prescription | Type: HUMAN PRESCRIPTION DRUG LABEL
Date: 20241128

ACTIVE INGREDIENTS: DYCLONINE HYDROCHLORIDE 5 mg/1 mL
INACTIVE INGREDIENTS: CHLOROBUTANOL 3 mg/1 mL; SODIUM CHLORIDE; HYDROCHLORIC ACID; WATER

DylcloPro
(Dyclonine Hydrochloride Topical Solution, USP, 0.5% and 1%)
Topical Anesthetic
Rx only

Description:

DycloPro (Dyclonine Hydrochloride Topical Solution, USP, 0.5% and 1%) topical anesthetics contain a local anesthetic agent and are administered topically. See INDICATIONS for specific uses.

DycloPro (Dyclonine Hydrochloride Topical Solution, USP, 0.5% and 1%) contain dyclonine HCl, which is chemically designated as 4’-butoxy-3-piperidinopropiophenone HCl. Dyclonine HCl is a white crystalline powder that is sparingly soluble in water and has the following structural formula:

COMPOSITION OF Dyclonine HCl Topical Solution, USP, 0.5% and 1% topical anesthetics:

Each mL of Dyclonine HCl Topical Solution, USP, 0.5% contains dyclonine HCl, 5 mg.
Each mL of Dyclonine HCl Topical Solution, USP, 1% contains dyclonine HCl, 10 mg.
Both solutions also contain chlorbutanol hydrous and sodium chloride, and the pH is adjusted 3.0-5.0 by means of hydrochloric acid.

CLINICAL PHARMACOLOGY:

Dyclonine HCl Topical Solution, USP effects surface anesthesia when applied topically to mucous membranes. Effective anesthesia varies with different patients, but usually occurs from 2 to 10 minutes after application and persists for approximately 30 minutes.

INDICATIONS AND USAGE:

Dyclonine HCl Topical Solution, USP is indicated for anesthetizing accessible mucous membranes (e.g., the mouth, pharynx, larynx, trachea, esophagus, and urethra) prior to various endoscopic procedures.

Dyclonine HCl Topical Solution, USP, 0.5% topical anesthetic may also be used to block the gag reflex, to relieve the pain of oral ulcers or stomatitis and to relieve pain associated with ano-genital lesions.

CONTRAINDICATIONS:

Dyclonine HCl Topical Solution, USP is contraindicated in patients known to be hypersensitive (allergic) to the local anesthetic or to other components of Dyclonine HCl Topical Solution, USP.

WARNINGS:

IN ORDER TO MANAGE POSSIBLE ADVERSE REACTIONS, RESUSCITATIVE EQUIPMENT, OXYGEN AND OTHER RESUSCITATIVE DRUGS SHOULD BE IMMEDIATELY AVAILABLE WHENEVER LOCAL ANESTHETIC AGENTS, SUCH AS DYCLONINE, ARE ADMINISTERED TO MUCOUS MEMBRANES.

Dyclonine HCl Topical Solution, USP should not be injected into tissue or used in the eyes because of highly irritant properties.

Dyclonine HCl Topical Solution, USP should be used with extreme caution in the presence of sepsis or severely traumatized mucosa in the area of application since under such conditions there is the potential for rapid systemic absorption.

PRECAUTIONS:

General: The safety and effectiveness of dyclonine depend on proper dosage, correct technique, adequate precautions, and readiness for emergencies (see WARNINGS and ADVERSE REACTIONS). The lowest dosage that results in effective anesthesia should be used to avoid high plasma levels and serious adverse effects. Repeated doses of dyclonine may cause significant increases in blood levels with each repeated dose because of slow accumulation of the drug or its metabolites. Tolerance to elevated blood levels varies with the status of the patient. Debilitated, elderly patients, acutely ill patients and children should be given reduced doses commensurate with their age, weight and physical condition. Dyclonine should also be used with caution in patients with severe shock or heart block.

Dyclonine HCl Topical Solution, USP should be used with caution in persons with known drug sensitivities.

Information for Patients:

When topical anesthetics are used in the mouth or throat, the patient should be aware that the production of topical anesthesia may impair swallowing and thus enhance the danger of aspiration. For this reason, food should not be ingested for 60 minutes following use of local anesthetic preparations in the mouth or throat area. This is particularly important in children because of their frequency of eating.

Numbness of the tongue or buccal mucosa may increase the danger of biting trauma. When Dyclonine HCl Topical Solution, USP is used to relieve the pain of oral ulcers or stomatitis which interferes with eating, patients should be warned about the risk of biting trauma before they accept this treatment; caution should be exercised in selecting food and eating. Following other uses in the mouth and throat area, food and/or chewing gum should not be used while the area is anesthetized.

Drug/Laboratory Test Interactions:

Dyclonine HCl Topical Solution, USP should not be used in cystoscopic procedures following intravenous pyelography because an iodine precipitate occurs which interferes with visualization.

Carcinogenesis, mutagenesis, impairment of fertility:

Long-term animal studies have not been performed to evaluate the potential mutagenic or carcinogenic potential of dyclonine hydrochloride. Likewise, animal studies to characterize the potential effects of dyclonine hydrochloride on fertility have not been completed.

Pregnancy: Teratogenic Effects:

Pregnancy Category C. Animal reproduction studies have not been conducted with dyclonine hydrochloride. It is also not known whether dyclonine hydrochloride can cause fetal harm when administered to a pregnant woman or can affect reproduction capacity. Dyclonine hydrochloride should be given to pregnant women only if clearly needed.

Nursing Mothers:

It is not known whether this drug is excreted in human milk. Because many drugs are excreted in human milk, caution should be exercised when dyclonine is administered to a nursing woman.

Pediatric Use:

Safety and effectiveness in children under the age of 12 have not been established.

ADVERSE REACTIONS:

Adverse experiences following the administration of dyclonine are similar in nature to those observed with other local anesthetic agents. These adverse experiences are, in general, dose-related and may result from high plasma levels caused by excessive dosage or rapid absorption, or may result from a hypersensitivity, idiosyncrasy or diminished tolerance on the part of the patient. Serious adverse experiences are generally systemic in nature. The following types are those most commonly reported:

Central nervous system:

CNS manifestations are excitatory and/or depressant and may be characterized by lightheadedness, nervousness, apprehension, euphoria, confusion, dizziness, drowsiness, tinnitus, blurred or double vision, vomiting, sensations of heat, cold or numbness, twitching, tremors, convulsions, unconsciousness, respiratory depression and arrest. The excitatory manifestations may be very brief or may not occur at all, in which case the first manifestation of toxicity may be drowsiness merging into unconsciousness and respiratory arrest.

Drowsiness following the administration of dyclonine is usually an early sign of a high blood level of the drug and may occur as a consequence of rapid absorption.

Cardiovascular system:

Cardiovascular manifestations are usually depressant and are characterized by bradycardia, hypotension, and cardiovascular collapse, which may lead to cardiac arrest.

Allergic:

Allergic reactions are characterized by cutaneous lesions, urticaria, edema or anaphylactoid reactions. Allergic reactions may occur as a result of sensitivity either to the local anesthetic agent or to the other ingredients used in this formulation. Allergic reactions, if they occur, should be managed by conventional means. The detection of sensitivity by skin testing is of doubtful value. Local reactions include irritation, stinging, urethritis with and without bleeding.

OVERDOSAGE:

Acute emergencies from local anesthetics are generally related to high plasma levels encountered during therapeutic use of local anesthetics. (See ADVERSE REACTIONS, WARNINGS and PRECAUTIONS).

Management of local anesthetic emergencies: The first consideration is prevention, best accomplished by careful and constant monitoring of cardiovascular and respiratory vital signs and the patient’s state of consciousness after each local anesthetic administration.

The first step in the management of convulsions consists of immediate attention to the maintenance of a patent airway and assisted or controlled ventilation with oxygen and a delivery system capable of permitting immediate positive airway pressure by mask. Immediately after the institution of these ventilatory measures, the adequacy of the circulation should be evaluated, keeping in mind that drugs used to treat convulsions sometimes depress the circulation when administered intravenously. Should convulsions persist despite adequate respiratory support, and if the status of the circulation permits, small increments of an ultra-short acting barbiturate (such as thiopental or thiamylal) or a benzodiazepine (such as diazepam) may be administered intravenously. The clinician should be familiar, prior to use of local anesthetics, with these anticonvulsant drugs. Supportive treatment of circulatory depression may require administration of intravenous fluids and, when appropriate, a vasopressor as directed by the clinical situation (e.g., ephedrine).

If not treated immediately, both convulsions and cardiovascular depression can result in hypoxia, acidosis, bradycardia, arrhythmias and cardiac arrest. If cardiac arrest should occur, standard cardiopulmonary resuscitative measures should be instituted.

The median lethal dose (LD50) of Dyclonine HCl Topical Solution, USP administered orally to female rats is 176 mg/kg and 90 mg/kg in female mice. Intraperitoneally the LD50 in female rats is 31 mg/kg and 43 mg/kg in female mice.

DOSAGE AND ADMINISTRATION:

As with all local anesthetics, the dosage varies and depends upon the area to be anesthetized, vascularity of the tissues, individual tolerance and the technique of anesthesia. The lowest dosage needed to provide effective anesthesia should be administered.

A maximum dose of 30 mL of Dyclonine HCl Topical Solution, USP 1% topical anesthetic (300 mg of dyclonine HCl) may be used, although satisfactory anesthesia is usually produced within the range of 4 to 20 mL. For specific techniques and procedures refer to standard textbooks.

Although as much as 300 mg of Dyclonine HCl Topical Solution USP (as a 1% solution) have been tolerated, this dosage as a 0.5% solution has not been administered primarily because satisfactory anesthesia in endoscopic procedures can usually be produced by lesser amounts. For specific techniques for endoscopic procedures refer to standard textbooks.

Dyclonine HCl Topical Solution, USP can be used for a period of 7 days after open.

PROCTOLOGY:

Apply pledgets of cotton or sponges moistened with the Dyclonine HCl Topical Solution, USP 0.5% to postoperative wounds for the relief of discomfort and pain.

GYNECOLOGY:

Apply Dyclonine HCl Topical Solution, USP 0.5% as wet compresses or as a spray to relieve the discomfort of episiotomy or perineorrhaphy wounds.

ONCOLOGY-RADIOLOGY:

Apply Dyclonine HCl Topical Solution, USP 0.5% as a rinse or swab to inflamed or ulcerated mucous membrane of the mouth caused by anti-neoplastic chemotherapy or radiation therapy. In lesions of the esophagus, 5-15 mL of the anesthetic may be swallowed to relieve pain and allow more comfortable deglutition.

OTORHINOLARYNGOLOGY:

To suppress the gag reflex and to facilitate examination of the posterior pharynx or larynx, apply Dyclonine HCl Topical Solution, USP, 0.5% as a spray or gargle.

Dyclonine HCl Topical Solution, USP, 0.5% may be applied as a rinse or swab to relieve the discomfort of aphthous stomatitis, herpetic stomatitis, or other painful oral lesions.

DENTISTRY:

Dyclonine HCl Topical Solution, USP, 0.5% topical anesthetic is useful to suppress the gag reflex in the positioning of x-ray films, making prosthetic impressions, and doing surgical procedures in the molar areas. It is also useful as a preinjection mucous membrane anesthetic or applied to the gums prior to scaling (prophylaxis). The anesthetic can be applied as a mouthwash or gargle and the excess spit out.

HOW SUPPLIED:

Clear and colorless sterile solution, in one fluid ounce bottles.
Multi dose
Dyclonine HCl Topical Solution 0.5% (NDC 0362-3971-05)
Dyclonine HCl Topical Solution 1% (NDC 0362-3918-10).
Store at 20° to 25°C (68° to 77°F) [see USP Controlled Room Temperature]. Keep upright and preserve in tight and light-resistant container. Avoid excessive heat (temperatures above 40ºC [104ºF]). Subject to damage by freezing.

Manufactured for SEPTODONT, Inc.
205 Granite Run Dr., Suite 150,
Lancaster, PA, USA 17601
by Novocol Pharmaceutical of Canada, Inc.
Ontario, Canada N1R 6X3

Rev. 06/2024 (2814-1)

Principal Display Panel - Carton - 0.5%

NDC 0362-3971-05

DycloPro

(Dyclonine Hydrochloride Topical Solution, USP, 0.5%)

Topical Anesthetic

1FL.OZ. (30mL)

NOT FOR INJECTION

NOT FOR USE IN THE EYES.

Rx only

Multi dose

Manufactured for SEPTODONT, Inc.

205 Granite Run Dr., Suite 150,

Lancaster, PA, USA 17601

by Novocol Pharmaceutical of Canada, Inc.

Ontario, Canada N1R 6X3